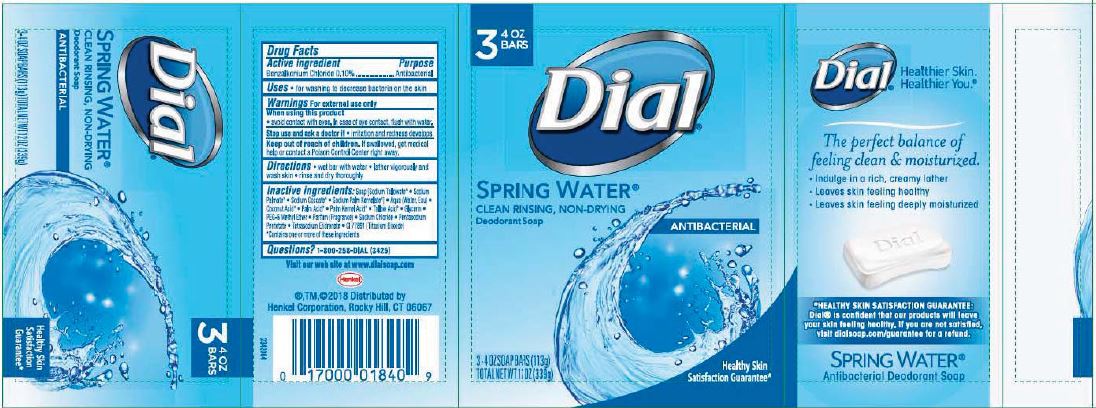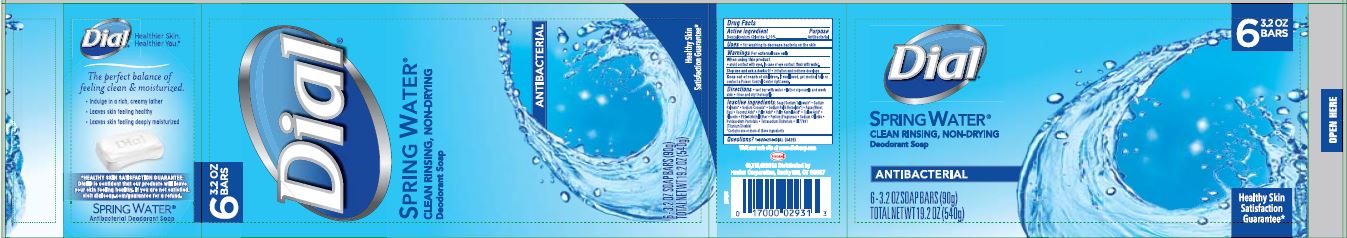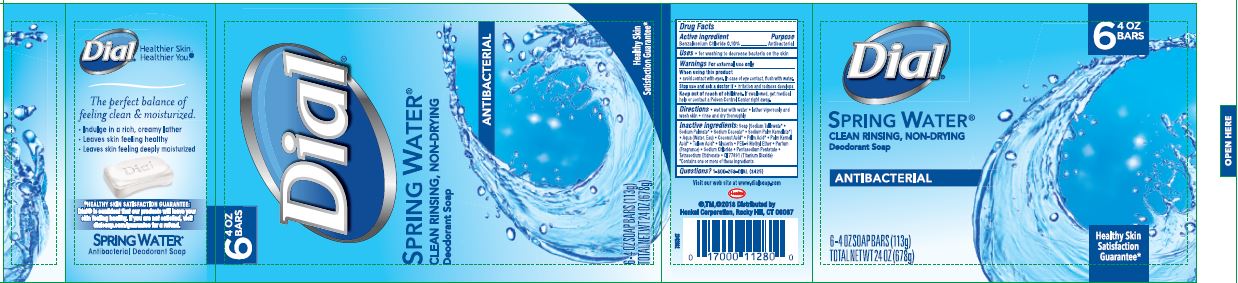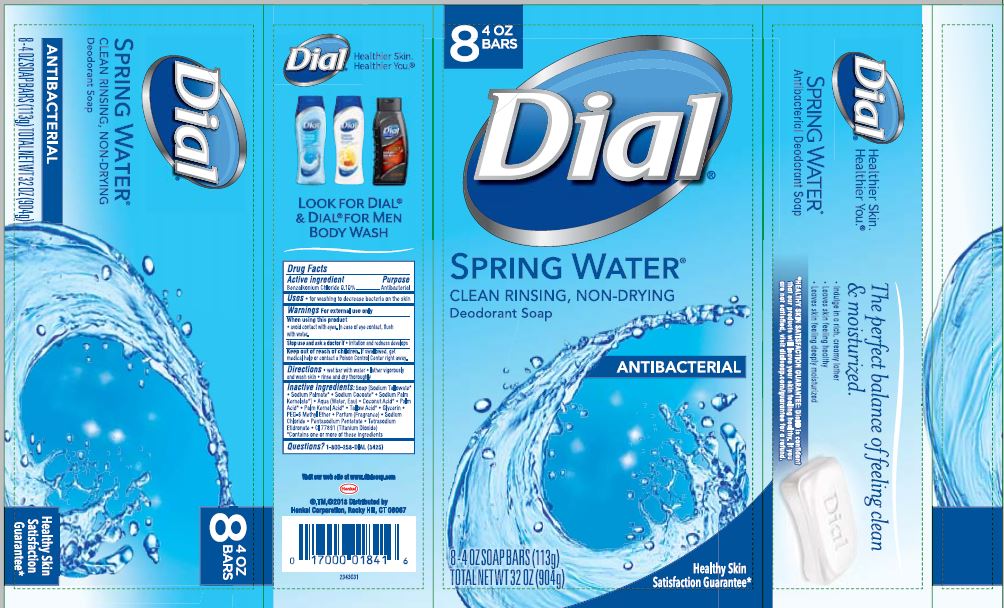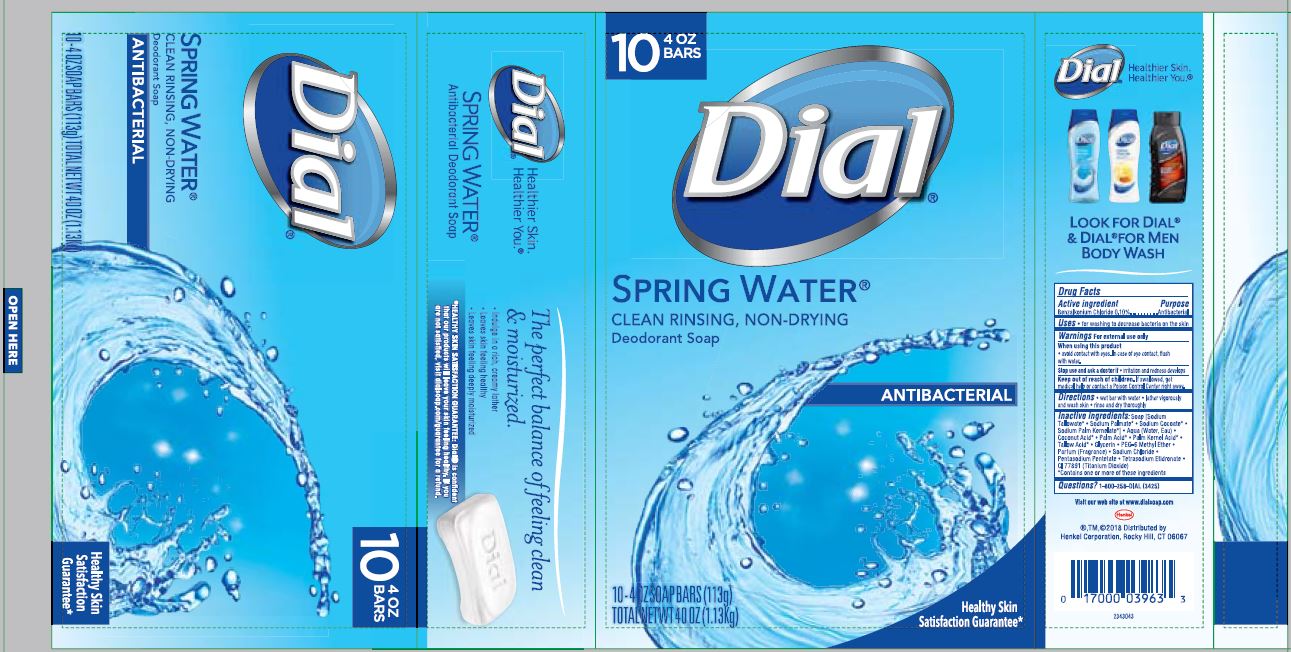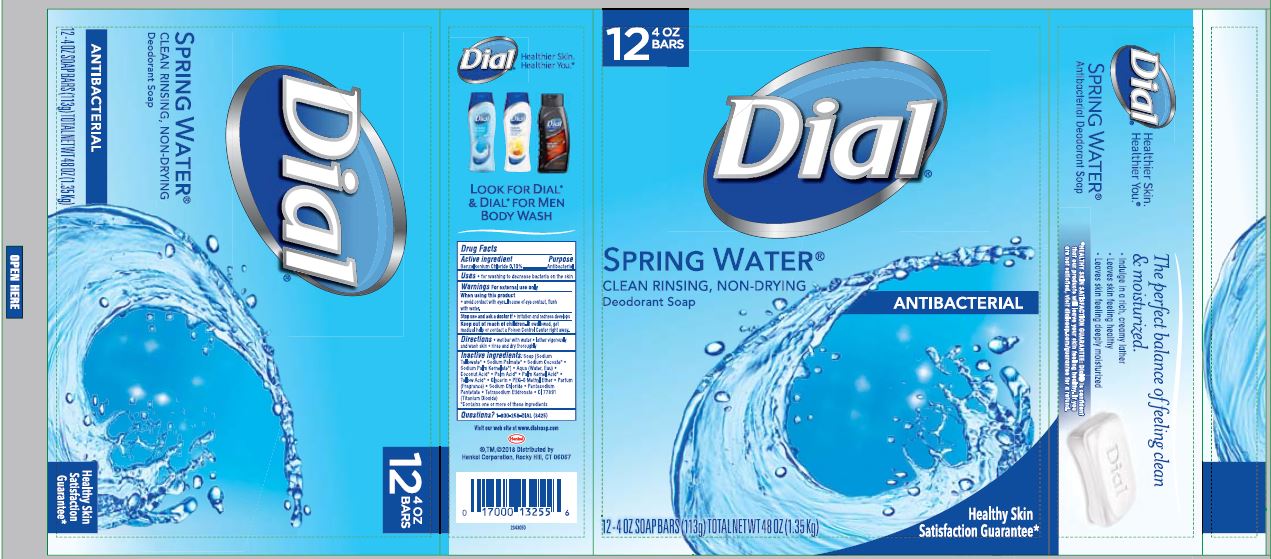 DRUG LABEL: Dial Antibacterial Bar
NDC: 54340-276 | Form: SOAP
Manufacturer: Henkel Corporation
Category: otc | Type: HUMAN OTC DRUG LABEL
Date: 20200103

ACTIVE INGREDIENTS: BENZALKONIUM CHLORIDE 0.1 g/100 g
INACTIVE INGREDIENTS: SODIUM TALLOWATE, BEEF 59.1 g/100 g

Dial Antibacterial Bar Soap - Spring Water

Active ingredient

Benzalkonium Chloride 0.10%

Purpose

Antibacterial

Uses

- for washing to decrease bacteria on the skin.

Warnings

For external use only

When using this product

- avoid contact with eyes. In case of eye contact, flush with water.

Stop use and ask a doctor if

- irritation and redness defelops

Keep out of reach of children.

If swallowed, get medical help or contact Poison Control Center right away.

Directions

- wet bar with water
- lather vigorously and wash skin
- rinse and dry thoroughly

Inactive ingredients

Soap [Sodium Tallowate* • Sodium Palmate* • Sodium Cocoate* • Sodium Palm Kernelate*] • Aqua (Water, Eau) • Coconut Acid* • Palm Acid* • Palm Kernel Acid* • Tallow Acid* • Glycerin • PEG-6 Methyl Ether • Parfum (Fragrance) • Sodium Chloride • Pentasodium Pentetate • Tetrasodium Etidronate • CI 77891 (Titanium Dioxide)

*Contains one or more of these ingredients

Questions?

1-800-258-DIAL (3425)